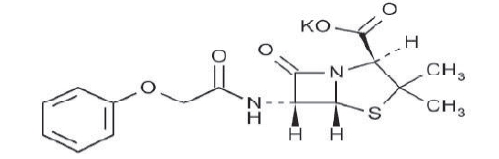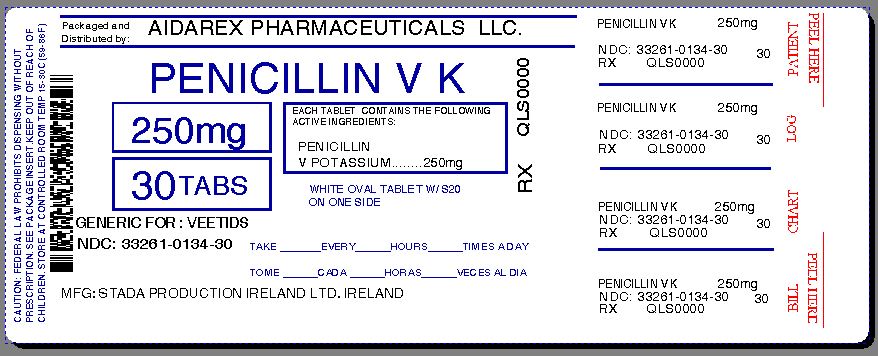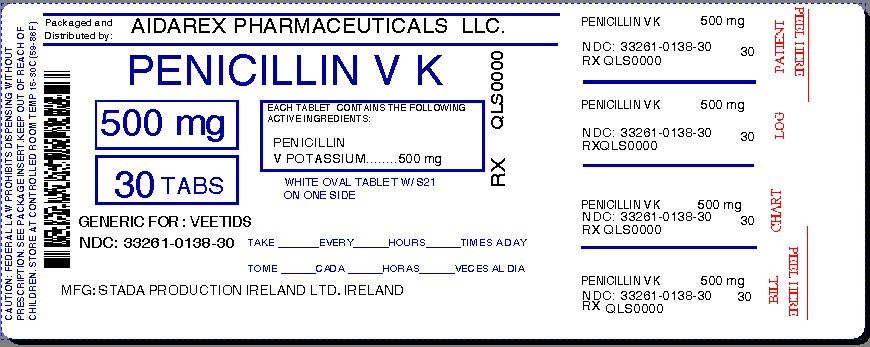 DRUG LABEL: Penicillin V Potassium
NDC: 33261-134 | Form: TABLET
Manufacturer: Aidarex Pharmaceuticals LLC
Category: prescription | Type: HUMAN PRESCRIPTION DRUG LABEL
Date: 20140123

ACTIVE INGREDIENTS: PENICILLIN V POTASSIUM 250 mg/1 1
INACTIVE INGREDIENTS: LACTOSE; MAGNESIUM STEARATE; CELLULOSE, MICROCRYSTALLINE; POVIDONES; SODIUM LAURYL SULFATE; POLYETHYLENE GLYCOLS

Penicillin V Potassium Tablets, USP - 250 mg and 500 mg
Penicillin V Potassium for Oral Solution, USP - 125 mg/5 mL and 250 mg/5 mL
Rx Only

To reduce the development of drug-resistant bacteria and maintain the effectiveness of Penicillin V Potassium Tablets, Penicillin V Potassium for Oral Solution and other antibacterial drugs, Penicillin V Potassium Tablets and Penicillin V Potassium for Oral Solution should be used only to treat or prevent infections that are proven or strongly suspected to be caused by bacteria.

DESCRIPTION

Penicillin V is the phenoxymethyl analog of penicillin G. Penicillin V potassium is the potassium salt of penicillin V. Penicillin V Potassium is designated chemically as 4-Thia-1-azabicyclo [3.2.0] heptane-2-carboxylic acid, 3,3-dimethyl-7-oxo- 6-[(phenoxyacetyl)amino]-, monopotassium salt, [2S-(2α,5α,6β)]-. It has the following chemical structure:

The molecular formula is C16H17KN2O5S, and the molecular weight is 388.48.

Each tablet contains Penicillin V Potassium equivalent to 250 mg or 500 mg (400,000 or 800,000 units) of penicillin V.

Each Penicillin V Potassium tablet, USP, 250 mg contains 0.73 mEq (28.2 mg) of Potassium and each Penicillin V potassium tablet, USP, 500 mg contains 1.46 mEq (56.4 mg) of Potassium.

Each tablet also contains the following inactive ingredients: lactose, NF; magnesium stearate, NF; microcrystalline cellulose, NF; polyethylene glycol, NF; povidone, USP; sodium laurel sulfate, NF.

Each 5 mL when reconstituted as directed contains Penicillin V Potassium equivalent to 125 mg or 250 mg (200,000 or 400,000 units) of Penicillin V.

Each 5 mL of reconstituted Penicillin V Potassium for Oral Solution, USP,125 mg per 5 mL contains 0.42 mEq (16.4 mg) of Potassium. Each 5 mL of reconstituted Penicillin V Potassium for Oral Solution, USP, 250 mg per 5 mL contains 0.85 mEq (32.8 mg) of Potassium.

Each 5 mL of reconstituted suspension also contains the following inactive ingredients: aspartame, NF; citric acid, USP; FD&C Red No. 40; flavors; primary taste modifier; saccharin sodium, USP; silicon dioxide, NF; sodium citrate, USP; sodium propionate, NF; sucrose, NF.

CLINICAL PHARMACOLOGY

Penicillin V exerts a bactericidal action against penicillin-sensitive microorganisms during the stage of active multiplication. It acts through the inhibition of bisynthesis of cell wall mucopeptide. It is not active against the penicillinase-producing bacteria, which include many strains of staphylococci. The drug exerts high in vitro activity against staphylococci (except penicillinase-producing strains), streptococci (groups A, C, G, H, L and M) and pneumococci. Other organisms sensitive in vitro to penicillin V are Corynebacterium diphtheriae, Bacillus anthracis, Clostridia, Actinomyces bovis, Streptobacillus moniliformis, Listeria monocytogenes, Leptospira and N. gonorrhoeae. Treponema pallidum is extremely sensitive.

The potassium salt of penicillin V has the distinct advantage over penicillin G in resistance to inactivation by gastric acid. It may be given with meals; however, blood levels are slightly higher when the drug is given on an empty stomach. Average blood levels are two to five times higher than the levels following the same dose of oral penicillin G and also show much less individual variation.

Once absorbed, penicillin V is about 80% bound to serum protein. Tissue levels are highest in the kidneys, with lesser amounts in the liver, skin, and intestines. Small amounts are found in all other body tissues and cerebrospinal fluid. The drug is excreted as rapidly as it is absorbed in individuals with normal kidney function; however, recovery of the drug from the urine indicates that only about 25% of the dose given is absorbed. In neonates, young infants, and individuals with impaired kidney function, excretion is considerably delayed.

INDICATIONS AND USAGE

To reduce the development of drug-resistant bacteria and maintain the effectiveness of Penicillin V Potassium Tablets, Penicillin V Potassium for Oral Solution and other antibacterial drugs, Penicillin V Potassium Tablets, and Penicillin V Potassium for Oral Solution should be used only to treat or prevent infections that are proven or strongly suspected to be caused by susceptible bacteria. When culture and susceptibility information are available, they should be considered in selecting or modifying antimicrobial therapy.

In the absence of such data, local epidemiology and susceptibility patterns may contribute to the empiric selection of therapy.

Penicillin V Potassium Tablets, USP and Penicillin V Potassium for Oral Solution, USP, are indicated in the treatment of mild to moderately severe infections due to penicillin G sensitive microorganisms. Therapy should be guided by bacteriological studies (including sensitivity tests) and by clinical response.

NOTE: Severe pneumonia, empyema, bacteremia, pericarditis, meningitis, and arthritis should not be treated with penicillin V during the acute stage.

Indicated surgical procedures should be performed.

The following Infections will usually respond to adequate dosage of Penicillin V:

Streptococcal infections (without bacteremia): Mild to moderate infections of the upper respiratory tract, scarlet fever and mild erysipelas.

NOTE: Streptococci in groups A, C, G, H, L, and M are very sensitive to penicillin. Other groups, including group D (enterococcus) are resistant.

Pneumococcal infections: Mild to moderately severe infections of the respiratory tract.

Staphylococcal infections - penicillin G sensitive: Mild infections of the skin and soft tissues.

NOTE: Reports indicate an increasing number of strains of staphylococci resistant to penicillin G, emphasizing the need for culture and sensitivity studies in treating suspected staphylococcal infections.

Fusospirochetosis (Vincent's gingivitis and pharyngitis): Mild to moderately severe infections of the oropharynx usually respond to therapy with oral penicillin.

NOTE: Necessary dental care should be accomplished in infections involving the gum tissue.

Medical conditions in which oral penicillin therapy is indicated as prophylaxis:

For the prevention of recurrence following rheumatic fever and/or chorea: Prophylaxis with oral penicillin on a continuing basis has proven effective in preventing recurrence of these conditions.

Although no controlled clinical efficacy studies have been conducted, penicillin V has been suggested by the American Heart Association and the American Dental Association for use as an oral regimen for prophylaxis against bacterial endocarditis in patients with congenital heart disease or rheumatic or other acquired valvular heart disease when they undergo dental procedures and surgical procedures of the upper respiratory tract.^1 Oral penicillin should not be used in those patients at particularly high risk for endocarditis (e.g. those with prosthetic heart valves or surgically constructed systemic pulmonary shunts). Penicillin V should not be used as adjunctive prophylaxis for genitourinary instrumentation or surgery, lower-intestinal tract surgery, sigmoidoscopy, and childbirth. Since it may happen that alpha haemolytic streptococci relatively resistant to penicillin may be found when patients are receiving continuous oral penicillin for secondary prevention of rheumatic fever, prophylactic agents, other than penicillin may be chosen for these patients and prescribed in addition to their continuous rheumatic fever prophylactic regimen.

NOTE: When selecting antibiotics for the prevention of bacterial endocarditis, the physician or dentist should read the full joint statement of the American Heart Association and the American Dental Association.^1

CONTRAINDICATIONS

A previous hypersensitivity reaction to any penicillin is a contraindication.

WARNINGS

SERIOUS AND OCCASIONALLY FATAL HYPERSENSITIVITY (ANAPHYLACTIC) REACTIONS HAVE BEEN REPORTED IN PATIENTS ON PENICILLIN THERAPY. THESE REACTIONS ARE MORE LIKELY TO OCCUR IN INDIVIDUALS WITH A HISTORY OF PENICILLIN HYPERSENSITIVITY AND/OR A HISTORY OF SENSITIVITY TO MULTIPLE ALLERGENS. THERE HAVE BEEN REPORTS OF INDIVIDUALS WITH A HISTORY OF PENICILLIN HYPERSENSITIVITY WHO HAVE EXPERIENCED SEVERE REACTIONS WHEN TREATED WITH CEPHALOSPORINS. BEFORE INITIATING THERAPY WITH PENICILLIN V POTASSIUM, CAREFUL INQUIRY SHOULD BE MADE CONCERNING PREVIOUS HYPERSENSITIVITY REACTION TO PENICILLINS, CEPHALOSPORINS, OR OTHER ALLERGENS. IF AN ALLERGIC REACTION OCCURS, PENICILLIN V POTASSIUM SHOULD BE DISCONTINUED AND APPROPRIATE THERAPY INSTITUTED. SERIOUS ANAPHYLACTOID REACTIONS REQUIRE IMMEDIATE EMERGENCY TREATMENT WITH EPINEPHRINE. OXYGEN, INTRAVENOUS STEROIDS, AND AIRWAY MANAGEMENT, INCLUDING INTUBATION, SHOULD ALSO BE ADMINISTERED AS INDICATED.

Clostridium difficile associated diarrhea (CDAD) has been reported with use of nearly all antibacterial agents, including Penicillin V Potassium Tablets and Penicillin V Potassium for Oral Solution, and may range in severity from mild diarrhea to fatal colitis. Treatment with antibacterial agents alters the normal flora of the colon leading to overgrowth of C. difficile.

C. difficile produces toxins A and B which contribute to the development of CDAD. Hypertoxin producing strains of C. difficile cause increased morbidity and mortality, as these infections can be refractory to antimicrobial therapy and may cause colectomy. CDAD must be considered in all patients who present with diarrhea following antibiotic use. Careful medical history is necessary since CDAD has been reported to occur over two months after the administration of antibacterial agents.

If CDAD is suspected or confirmed, ongoing antibiotic use not directed against C. difficile may need to be discontinued. Appropriate fluid and electrolyte management, protein supplementation, antibiotic treatment of C. difficile, and surgical evaluation should be instituted as clinically indicated.

PRECAUTIONS

General

Penicillin should be used with caution in individuals with histories of significant allergies and/or asthma.

Prescribing Penicillin V Potassium Tablets and Penicillin V Potassium for Oral Solution in the absence of a proven or strongly suspected bacterial infection of a prophylactic indication is unlikely to provide benefit to the patient and increases the risk of the development of drug-resistant bacteria.

The oral route of administration should not be relied upon in patients with severe illness, or with nausea, vomiting, gastric dilatation, cardiospasm or intestinal hypermotility.

Occasionally patients will not absorb therapeutic amounts of orally administered penicillin.

In streptococcal infections, therapy must be sufficient to eliminate the organism (ten-day minimum): otherwise the sequelae of streptococcal disease may occur. Cultures should be taken following completion of treatment to determine whether streptococci have been eradicated.

Prolonged use of antibiotics may promote the overgrowth of nonsusceptible organisms, including fungi. Should superinfection occur, appropriate measures should be taken.

Oral Solutions contain aspartame. Phenylketonurics: Both the 125 mg and 250 mg Oral Solutions contain phenylalanine 4.5 mg per 5 mL.

Information for Patients

Patients should be counseled that antibacterial drugs, including Penicillin V Potassium Tablets and Penicillin V Potassium for Oral Solution should only be used to treat bacterial infections. They do not treat viral infections (e.g. the common cold).

When Penicillin V Potassium Tablets or Penicillin V Potassium Oral Solution are prescribed to treat a bacterial infection, patients should be told that although it is common to feel better early in the course of therapy, the medication should be taken exactly as directed. Skipping doses or not completing the full course of therapy may:

(i) Decrease the effectiveness of the immediate treatment, and

(ii) Increase the likelihood that bacteria will develop resistance and will not be treatable by the antibacterial drug product or other antibacterial drugs in the future.

Diarrhea is a common problem caused by antibiotics which usually ends when the antibiotic is discontinued. Sometimes after starting treatment with antibiotics, patients can develop watery and bloody stools (with or without stomach cramps and fever) even as late as two or more months after having taken the last dose of the antibiotic. If this occurs, patients should contact their physician as soon as possible.

ADVERSE REACTIONS

Although the incidence of reactions to oral penicillins has been reported with much less frequency than following parenteral therapy, it should be remembered that all degrees of hypersensitivity, including fatal anaphylaxis, have been reported with oral penicillin.

The most common reactions to oral penicillin are nausea, vomiting, epigastric distress, diarrhea, and black hairy tongue. The hypersensitivity reactions reported are skin eruptions (maculopapular to exfoliative dermatitis), urticaria and other serum sickness-like reactions, laryngeal edema and anaphylaxis.

Fever and eosinophilia may frequently be the only reaction observed. Hemolytic anemia, leukopenia, thrombocytopenia, neuropathy and nephropathy are infrequent reactions and usually associated with high doses of parenteral penicillin.

DOSAGE AND ADMINISTRATION

The dosage of penicillin V potassium tablets and penicillin V potassium for oral solution should be determined according to the sensitivity of the causative microorganisms and the severity of the infection, and adjusted to the clinical response of the patient.

The usual dosage recommendations for adults and children 12 years and over are as follows:

Streptococcal infections - mild to moderately severe - of the upper respiratory tract and including scarlet fever and erysipelas: 125 mg to 250 mg (200,000 to 400,000 units) every 6 to 8 hours for 10 days.

Pneumococcal infections - mild to moderately severe - of the respiratory tract, including otitis media: 250 mg to 500 mg (400,000 to 800,000 units) every 6 hours until the patient has been afebrile for at least 2 days.

Staphylococcal infections - mild infections of skin and soft tissue (culture and sensitivity tests should be performed): 250 mg to 500 mg (400,000 to 800,000 units) every 6 to 8 hours.

Fusospirochetosis (Vincent's infection) of the oropharynx. Mild to moderately severe infections: 250 mg to 500 mg (400,000 to 800,000 units) every 6 to 8 hours.

For the prevention of recurrence following rheumatic fever and/or chorea: 125 mg to 250 mg (200,000 to 400,000 units) twice daily on a continuing basis.

For prophylaxis against bacterial endocarditis^1 in patients with congenital heart disease or rheumatic or other acquired valvular heart disease when undergoing dental procedures or surgical procedures of the upper respiratory tract: 2 grams of penicillin V (1 gram for children under 60 lbs) 1 hour before the procedure, and then 1 gram (500 mg for children under 60 lbs) 6 hours later.

Directions for preparing oral solution

Prepare solution at the time of dispensing by adding the water in two portions to the bottle as follows: Loosen powder by tapping the bottle, add about half the water, and shake well. Add the remaining water and shake well to complete solution. Each teaspoon (5 mL) will contain Penicillin V Potassium equivalent to 125 mg or 250 mg of Penicillin V.

Product | Bottle; Size | Amount of water; required for; reconstitution
125 mg/5 mL | 100 mL | 65 mL
 | 200 mL | 127 mL
250 mg/5 mL | 100 mL | 65 mL
 | 200 mL | 127 mL

Note: Shake the oral solution well before using.

Store the reconstituted solution in a refrigerator. Discard any unused portion after 14 days. Keep the bottle tightly closed.

HOW SUPPLIED

Penicillin V Potassium Tablets, USP 250 mg (400,000 units) - White, oval, biconvex tablets engraved S20.

NDC 33261-0134-30 Bottles of 30

NDC 33261-0134-40 Bottles of 40

Penicillin V Potassium Tablets, USP 500 mg (800,000 units) - White, oval, biconvex tablets engraved S21.

NDC 33261-0138-20 Bottles of 20

NDC 33261-0138-28 Bottles of 28

NDC 33261-0138-30 Bottles of 30

NDC 33261-0138-40 Bottles of 40

Store at 20° to 25°C (68° to 77°F). [See USP Controlled Room Temperature]. Keep tightly closed. Protect from moisture.

REFERENCE

^1American Heart Association, 1984.

Prevention of bacterial endocarditis.

Circulation 70 (6): 1123A - 1127A.

Manufactured for:

DAVA Pharmaceuticals, Inc.

Fort Lee, NJ 07024, USA

by:

STADA Production Ireland Ltd.

Clonmel, Ireland.

Repackaged By :
Aidarex Pharmaceuticals LLC,
Corona, CA 92880

PACKAGE/LABEL PRINCIPAL DISPLAY PANEL

NDC 33261-0134-30

PENICILLIN V

POTASSIUM

TABLETS, USP

Equivalent to

250 mg

(400,000 units)

Penicillin V.

30 tablets Rx Only

250 mg equivalent to 400,000 units Penicillin V.

This is a bulk package, not intended for household use.

Dispense in a tight container as defined in the USP.

NDC 33261-0138-30

PENICILLIN V

POTASSIUM

TABLETS, USP

Equivalent to

500 mg

(800,000 units)

Penicillin V.

30 tablets Rx Only

500 mg equivalent to 800,000 units Penicillin V.

This is a bulk package, not intended for household use.

Dispense in a tight container as defined in the USP.

Usual Dosage - 250 to 500 mg (400,000 to 800,000 units)

every 6 to 8 hours. See package insert.

PHARMACY STOCK PACKAGE.

Store at 20°C to 25°C (68° to 77°F)

[See USP Controlled Room Temperature].

Keep tightly closed. Protect from moisture.

Manufactured for:

DAVA Pharmaceuticals, Inc.

Fort Lee, NJ 07024 USA

by:

STADA Production Ireland Ltd.

Clonmel, Ireland

Repackaged By :
Aidarex Pharmaceuticals LLC,
Corona, CA 92880

Rev. 04/10 0201G021